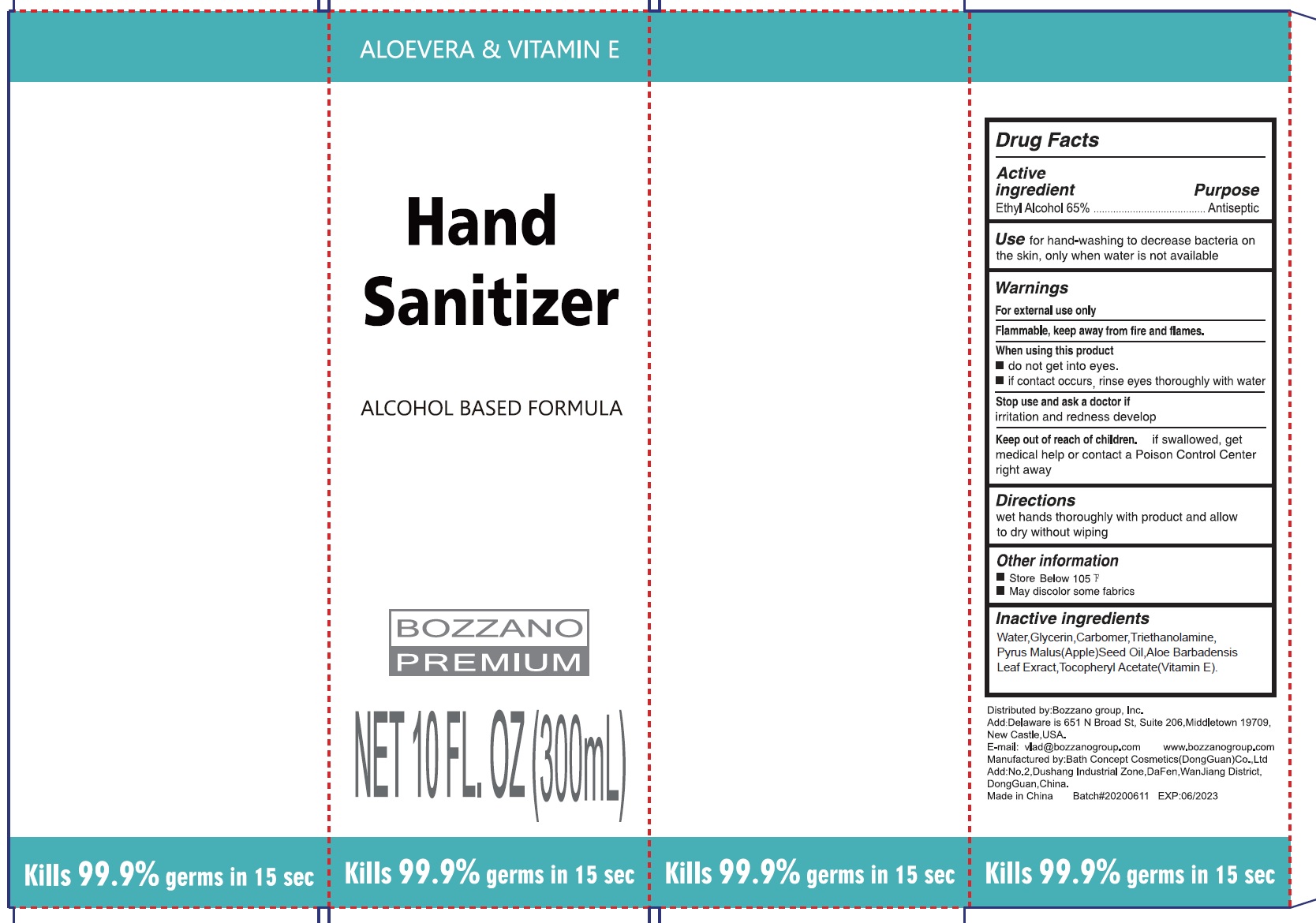 DRUG LABEL: Hand Sanitizer
NDC: 79396-000 | Form: GEL
Manufacturer: BOZZANO Group
Category: otc | Type: HUMAN OTC DRUG LABEL
Date: 20231026

ACTIVE INGREDIENTS: ALCOHOL 0.65 mL/1 mL
INACTIVE INGREDIENTS: WATER; GLYCERIN; CARBOMER HOMOPOLYMER, UNSPECIFIED TYPE; TROLAMINE; APPLE SEED OIL; ALOE VERA LEAF; .ALPHA.-TOCOPHEROL ACETATE

Hand Sanitizer

Active ingredient

Alcohol 65%

Purpose

Antiseptic

Use

for hand-washing to decrease bacteria on the skin, only when water is not available

Warnings

For external use only

Flammable, keep away from fire and flames.

When using this product

- do not get into eyes.
- if contact occurs, rinse eyes thoroughly with water

Stop use and ask a doctor if

irritation and redness develop

Keep out of reach of children.

if swallowed, get medical help or contact a Poison Control Center right away

Directions

Wet hands thoroughly with product and allow to dry without wiping

Other information

- Store Below 105 °F
- May discolor some fabrics

Inactive ingredients

Water,Glycerin,Fragrance,Carbomer,Triethanolamine,Pyrus Malus(Apple)Seed Oil,Aloe barbadensis Leaf Extract,Tocopheryl Acetate (Vitamin E).